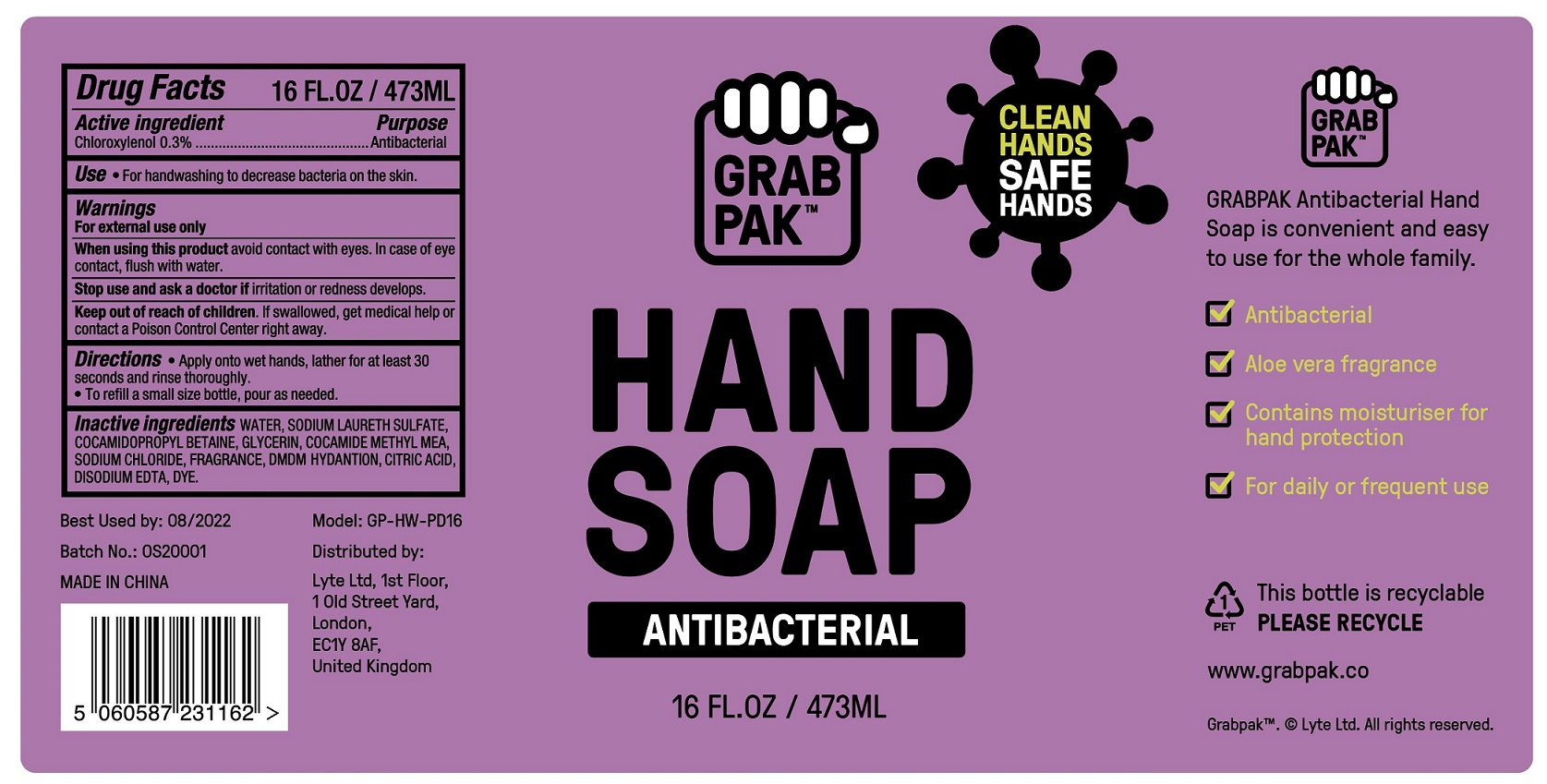 DRUG LABEL: Grabpak Antibacterial Hand
NDC: 80621-000 | Form: SOAP
Manufacturer: Lyte Ltd
Category: otc | Type: HUMAN OTC DRUG LABEL
Date: 20200921

ACTIVE INGREDIENTS: CHLOROXYLENOL 3 mg/1 mL
INACTIVE INGREDIENTS: WATER; SODIUM LAURETH SULFATE; COCAMIDOPROPYL BETAINE; GLYCERIN; COCOYL METHYL MONOETHANOLAMINE; SODIUM CHLORIDE; DMDM HYDANTOIN; CITRIC ACID MONOHYDRATE; EDETATE DISODIUM ANHYDROUS

Grabpak Antibacterial Hand Soap

Active ingredient

Chloroxylenol 0.3%

Purpose

Antibacterial

Use

For handwashing to decrease bacteria on the skin.

Warnings

For external use only

When using this product

avoid contact with eyes. In case of eye contact, flush with water.

Stop use and ask a doctor if

irritation or redness develops.

Keep out of reach of children.

If swallowed, get medical help or contact a Poison Control Center right away.

Directions

- Apply onto wet hands, lather for at least 30 seconds and rinse thoroughly.
- To refill a small size bottle, pour as needed.

Inactive ingredients

WATER, SODIUM LAURETH SULFATE, COCAMIDOPROPYL BETAINE, GLYCERIN, COCAMIDE METHYL MEA, SODIUM CHLORIDE, FRAGRANCE, DMDM HYDANTION, CITRIC ACID, DISODIUM EDTA, DYE.